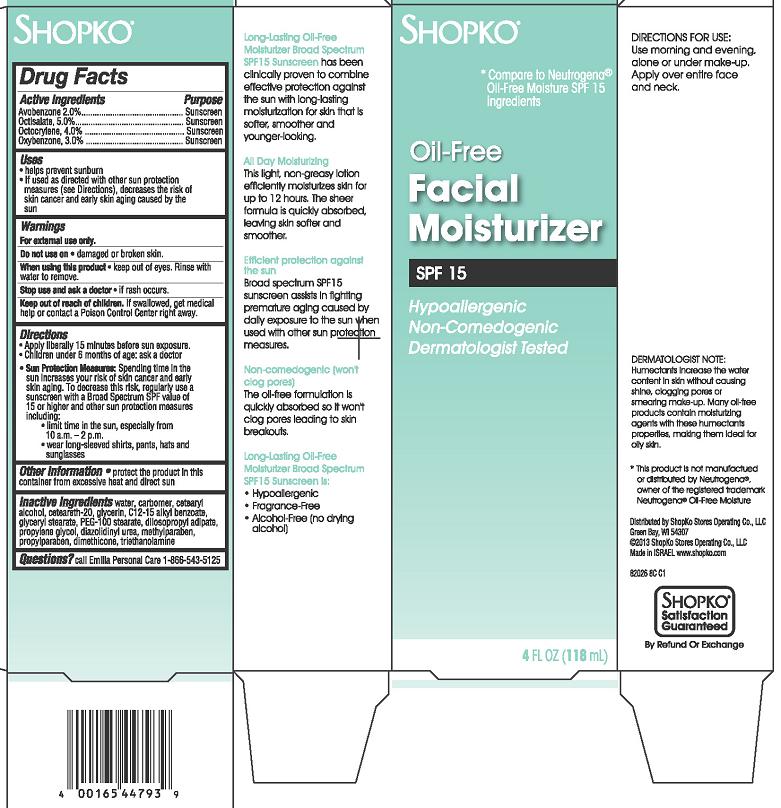 DRUG LABEL: Shopko Long Lasting Oil Free Moisturizer Broad Spectrum SPF15
NDC: 37012-026 | Form: CREAM
Manufacturer: Shopko Stores Operating Co., LLC
Category: otc | Type: HUMAN OTC DRUG LABEL
Date: 20130507

ACTIVE INGREDIENTS: AVOBENZONE 2 mg/100 mL; OCTISALATE 5 mg/100 mL; OCTOCRYLENE 4 mg/100 mL; OXYBENZONE 3 mg/100 mL
INACTIVE INGREDIENTS: WATER; CARBOMER HOMOPOLYMER TYPE C (ALLYL PENTAERYTHRITOL CROSSLINKED); CETOSTEARYL ALCOHOL; POLYOXYL 20 CETOSTEARYL ETHER; GLYCERIN; ALKYL (C12-15) BENZOATE; GLYCERYL MONOSTEARATE; PEG-100 STEARATE; DIISOPROPYL ADIPATE; PROPYLENE GLYCOL; DIAZOLIDINYL UREA; METHYLPARABEN; PROPYLPARABEN; DIMETHICONE; TROLAMINE

SHOPKO Long-Lasting Oil Free Moisturizer Broad Spectrum SPF 15

Active ingredient

Avobenzone 2.0%

Oclisalate 5.0%

Octocrylene 4.0%

Oxybenzone 3.0%

Purpose

Sunscreen

Uses

- helps prevent sunburn
- If used as directed with other sun protection measures (see Directions), decreases the risk of skin cancer and early skin aging caused by the sun

Warnings

For external use only.

Do not use on

- damaged or broken skin.

When using this product

- keep out of eyes. Rinse with water to remove.

Stop use and ask a doctor

- if rash occurs.

Keep Out of Reach of Children.

If swallowed, get medical help or contact a Poison Control Center right away.

Directions

- Apply liberally 15 minutes before sun exposure.
- Children under 6 months of age: ask a doctor
- Sun Protection Measures: Spending time in the sun increases your risk of skin cancer and early skin aging. To decrease this risk, regularly use a sunscreen with a Broad Spectrum SPF value of 15 or higher and other sun protection measures including:
  - limit time in the sun, especially from 10 a.m. - 2 p.m.
  - wear long-sleeved shirts, pants, hats and sunglasses

Other Information

- protect the product in this container from excessive heat and direct sun

Inactive Ingredients

water, carbomer, cetearyl alcohol, ceteareth-20, glycerin, C12-15 alkyl benzoate, glyceryl stearate, PEG-100 stearate, diisopropyl adipate, propylene glycol, diazolidinyl urea, methylparaben, propylparaben, dimethicone, triethanolamine.

Package/Label Principal Display Panel - Carton Label

Shopko*

*Compare to Neutrogena® Oil-Free Moisture SPF 15 Ingredients

Oil-Free Facial Moisturizer

With SPF 15

Hypoallergenic Non-Comedogenic Dermatologist Tested

4 FL OZ (118 mL)

Long-Lasting Oil-Free Moisturizer Broad Spectrum SPF15 Sunscreen has been clinically proven to combine effective protection against the sun with long-lasting moisturization for skin that is softer, smoother and younger-looking.

All Day Moisturizing
This light, non-greasy lotion efficiently moisturizes skin for up to 12 hours. The sheer formula is quickly absorbed, leaving skin softer and smoother.

Efficient protection against the sun
Broad spectrum SPF15 sunscreen assists in fighting premature aging caused by daily exposure to the sun when used with other sun protection measures.

Non-comedogenic (won't clog pores)
The oil-free formulation is quickly absorbed so it won't clog pores leading to skin breakouts.

Long-Lasting Oil-Free Moisturizer Broad Spectrum SPF 15 Sunscreen is:

- Hypoallergenic
- Fragrance-Free
- Alcohol-Free (no drying alcohol)

DIRECTIONS FOR USE:
Use morning and evening, alone or under make-up. Apply over entire face and neck.

DERMATOLOGIST NOTE:
Humectants increase the water content in skin without causing shine, clogging pores or smearing make-up. Many oil-free products contain moisturizing agents with these humectants properties, making them ideal for oily skin.

*This product is not manufactured or distributed by Neutrogena® owner of the registered trademark Neutrogena® Oil-Free Moisture

Distributed by ShopKo Stores Operating Co., LLC
Green Bay, WI 54307
© 2013 ShopKo Stores Operating Co., LLC
Made in Israel. www.shopko.com

82026 8C C1

SHOPKO* Satisfaction Guaranteed
By Refund or Exchange

Carton Label